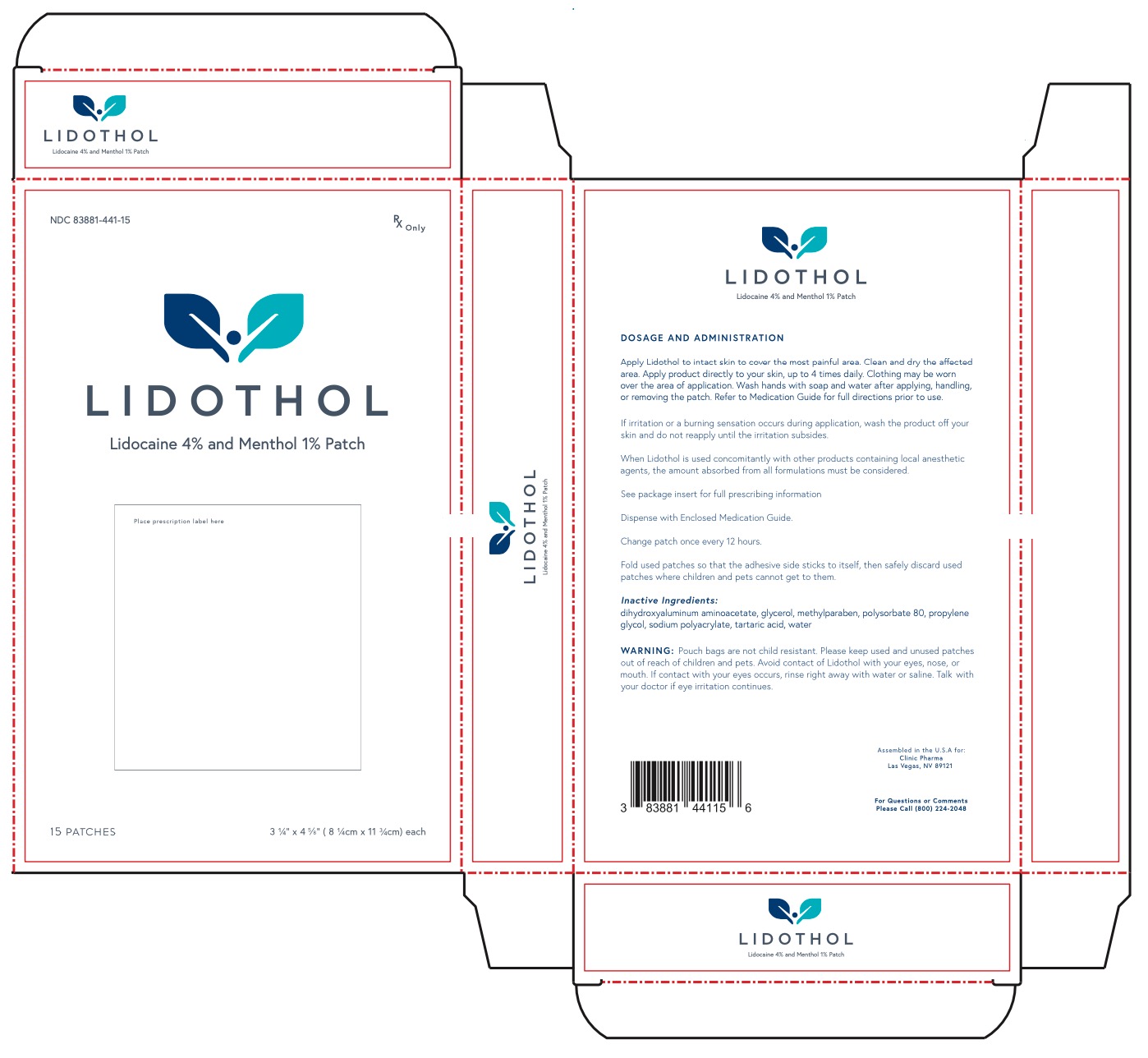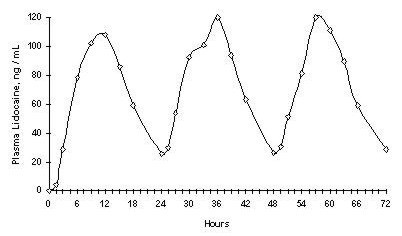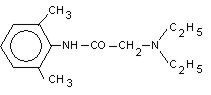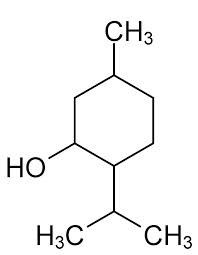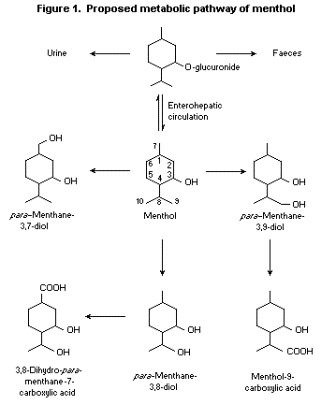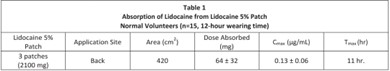 DRUG LABEL: LIDOTHOL
NDC: 83881-441 | Form: PATCH
Manufacturer: Clinic Pharma
Category: prescription | Type: HUMAN PRESCRIPTION DRUG LABEL
Date: 20260209

ACTIVE INGREDIENTS: MENTHOL 1 mg/100 mg; LIDOCAINE 4 mg/100 mg
INACTIVE INGREDIENTS: METHYLPARABEN; PROPYLENE GLYCOL; TARTARIC ACID; DIHYDROXYALUMINUM AMINOACETATE; GLYCERIN; POLYSORBATE 80; WATER; SODIUM POLYACRYLATE (8000 MW)

Lidothol Patch

DESCRIPTION:

Lidothol is a prescription topical patch, packaged with 15 medicated patches: 5 per re-sealable pouch, 3 pouches. Lidocaine is present in a 4% concentration (w/w). It is chemically designated as 2-‐(diethylamino)-‐N-‐(2,6-‐ dimethylphenyl) acetamide and has an empirical formula of C14H22N2O. The molecular weight of Lidocaine is 234.34 g/mol. Menthol is present in a 1% concentration (w/w). The chemical name is (1R,2S,5R)-‐2-‐isopropyl-‐5-‐methylcyclohexanol. The empirical formula for Menthol is C10H20O with a molecular weight of 156.27 g/mol.

Lidothol (Lidocaine 4% / Menthol 1% Patch) consists of an adhesive hydrogel containing Lidocaine 4% and Menthol 1%, applied to flexible woven polyester backing and protected by a plastic film. The protective film is removed prior to application to the skin. The size of the patch is 12cm x 8cm.

Lidocaine is chemically designated as 2-‐(diethylamino)-‐N-‐(2,6-‐dimethylphenyl), has an octanol: water partition ration of 43 at pH 7.4, and has the following structure:

Menthol is chemically designated as 2-‐Isopropyl-‐5-‐methylcyclohexanol. It contains colorless, hexagonal crystals, usually needle-‐like; fused masses or crystalline powder with a pleasant, peppermint-‐like odor. It has a melting point between 31°C to 36° C. Menthol has the following structure:

Each adhesive patch contains 76.5mg of Lidocaine and 85mg of Menthol. It also contains the following inactive ingredients:

dihydroxyaluminum aminoacetate, glycerol, methylparaben, polysorbate 80, propylene glycol, sodium polyacrylate, tartaric acid, water

CLINICAL PHARMACOLOGY:

Lidocaine is a topical anesthetic and stabilizes the neuronal membrane by inhibiting the ionic fluxes required for the initiation and conduction of impulses, thereby effecting local anesthetic action.

Menthol has local anesthetic and counterirritant qualities. It also acts as a weak kappa (ĸ) opioid receptor agonist. Menthol chemically triggers the cold-‐sensitive TRPM-‐8 receptors in the skin, which are responsible for the well-‐documented cooling sensation that occurs when applied to the skin. Menthol’s analgesic properties are not fully understood; however, they are mediated through a selective activation of ĸ-‐opioid receptors. Menthol also blocks voltage-‐sensitive sodium channels, reducing neural activity that may stimulate muscle tissue.

Pharmacodynamics

Menthol works by targeting the k-‐opiod receptor on the TRPM8 neuron. The TRPM8 neuron is normally activated at temperatures between (8° -‐ 28° C). Menthol causes the neuron to fire at temperatures above normal activation, which triggers the characteristic cooling sensation. Also because of Menthol's specific targeting of the k-‐opioid receptor, it is endowed with analgesic properties.

Lidocaine is an amide-‐type local anesthetic agent and is suggested to stabilize neuronal membranes by inhibiting the ionic fluxes required for the initiation and conduction of impulses.

The penetration of Lidocaine into intact skin after application of patch is sufficient to produce an analgesic effect, but less than the amount necessary to produce a complete sensory block.

Pharmacokinetics

Absorption:

The amount of Lidocaine and Menthol systemically absorbed is directly related to both the duration of application and the surface area over which it is applied.

In a pharmacokinetic study, three Lidocaine 5% patches were applied over an area of 420 cm2 of intact skin on the back of

normal volunteers for 12 hours. Blood samples were withdrawn for a determination of Lidocaine concentration during the application and for 12 hours after removal of patches. The results are summarized in table 1.

Repeated application of three days indicated that the Lidocaine concentration does not increase with daily use. The mean plasma pharmacokinetic profile for the 15 healthy volunteers is shown in Figure 1.When Lidocaine 5% patch is used according to the recommended dosing instructions, only 3 ± 2% of the dose applied is expected to be absorbed. At least 95% (665 mg) of Lidocaine will remain in a used patch. Mean peak blood concentration of Lidocaine is about 0.13 µg/mL (about 1/10 of the therapeutic concentration required to treat cardiac arrhythmias).

Figure 1

Mean Lidocaine blood concentrations after three consecutive daily applications of three Lidocaine 5% patches simultaneously for 12 hours per day in healthy volunteers (n = 15).

Distribution:

When Lidocaine is administered intravenously to healthy volunteers, the volume of distribution is 0.7 to 2.7 L/kg (mean 1.5

± 0.6 SD, n = 15). At concentrations produced by application of Lidocaine Patch 5%, Lidocaine is approximately 70% bound to plasma proteins, primarily alpha-‐1-‐acid glycoprotein. At much higher plasma concentrations (1 to 4 µg/mL of free base), the plasma protein binding of Lidocaine is concentration dependent. Lidocaine crosses the placental and blood brain barriers, presumably by passive diffusion.

Metabolism:

It is not known if Lidocaine is metabolized in the skin. Lidocaine is metabolized rapidly by the liver to a number of metabolites, including menoethylglycinexylidie (MEGX) and glycinexylidide (GX), both of which have pharmacologic activity similar to, but less potent than that of Lidocaine. A minor metabolite, 2,6-‐xylidine, has unknown pharmacologic activity but is carcinogenic in rats. The blood concentration of this metabolite is negligible following application of Lidocaine Patch 5%.

Following intravenous administration, MEGX and GX concentrations in serum range from 11% to 36% and from 5% to 11% of Lidocaine concentrations, respectively.

Humans rapidly metabolize Menthols primarily in the liver by the microsomes, using the enzyme CYP2A6. Cytochrome P450-‐mediated oxidation occurs in humans, yielding various alcohol and hydroxy acid derivatives. These are eliminated in the urine unchanged or conjugated with glucuronic acid.

Excretion:

Lidocaine and its metabolites are excreted by the kidneys. Less than 10% of Lidocaine is excreted unchanged. The half-‐life of Lidocaine elimination from plasma following IV administration is 81 to 149 minutes (mean 107 ± 22 SD, n=15). The systemic clearance is 0.33 to 0.90 L/min (mean 0.64 ± 0.18 SD, n=15).

Menthols are largely eliminated as glucuronides. In an experiment, 79% of a 1g (Quick, 1928) and 78% of a 10-‐20mg (Atzl et al., 1972) oral dose of Menthol was eliminated as the glucuronic acid conjugate within 6 h after administration to volunteers. Of a dose of 47 mg/kg bw [3-‐3H]-‐(-‐)-‐Menthol, 82% was eliminated in the urine 17 hours after administration.

Smaller amounts were distributed in the feces and ileum; only 1% of the activity remained in the liver (Clegg et al., 1982).

INDICATIONS AND USAGE:

Lidothol is a formulation used to assist patients in the treatment of mild to moderate acute or chronic aches or pain. Muscle or joint pain can be due to muscle or ligament strains, simple backache, tendonitis, osteoarthritis, rheumatoid arthritis, peripheral neuropathies such as diabetic neuropathy or post herpetic neuralgia, and other complex regional pains. It can also be used to help with certain types of headaches, but use with caution when applying in order to avoid eye contact.

Other uses may be considered if deemed clinically relevant.

CONTRAINDICATIONS:

Lidothol is contraindicated in patients with a known history of sensitivity to local anesthetics of the amide type, or to any other component of the product.

WARNINGS:

Excessive dosage or short interval between doses can result in high plasma levels and serious adverse effects. Patients should be instructed to strictly adhere to the recommended dosage and administration guidelines set forth in this literature and on your prescription label. The management of serious adverse reactions may require the use of resuscitative equipment, oxygen or other resuscitative drugs.

Accidental Exposure in Children

Even a used Lidothol patch contains a large amount of Lidocaine. The potential exists for a small child or a pet to suffer serious adverse effects from chewing or ingesting a new or used Lidothol patch, although the risk with this formulation has not been evaluated. It is important for patients to store and dispose of Lidothol beyond the reach of children, pets and others. (See HANDLING AND DISPOSAL)

Excessive Dosing

Excessive dosing by applying Lidothol to larger areas for longer than the recommended wearing time could result in increased absorption of Lidocaine and high blood concentrations, leading to serious adverse effects. Lidocaine toxicity could be expected at Lidocaine blood concentrations above 5 µg/mL. The blood concentration of Lidocaine is determined by the rate of systemic absorption and elimination. Longer duration of application, application of more than the recommended number of patches, smaller patients, or impaired elimination may all contribute to increasing the blood concentration of Lidocaine. With recommended dosing of Lidothol, the average blood concentration is about 0.13 µg/mL, but concentration higher than 0.25 µg/mL have been observed in some patients.

PRECAUTIONS:

Because of the possibility of sedation, patients should be cautioned regarding the use of heavy machinery or automobiles, also any activities made hazardous by decreased alertness.

Hepatic Disease

Patients with severe hepatic disease are at greater risk of developing toxic blood concentrations of Lidocaine, because of their inability to metabolize Lidocaine normally.

Allergic Reactions

Patients allergic to para-‐aminobenzoic acid derivatives (procaine, tetracaine, benzocaine, etc.) have not shown cross sensitivity to Lidocaine. However, Lidothol should be used with caution in patients with a history of drug sensitivities, especially if the etiologic agent is uncertain.

Non-intact Skin

Application to broken or inflamed skin, although not tested, may result in higher blood concentrations of Lidocaine from increased absorption. Lidothol is only recommended for use on intact skin.

Eye Exposure

The contact of Lidothol with eyes, although not studied, should be avoided based on the findings of severe eye irritations with the use of similar products in animals. If eye contact occurs, immediately wash out the eye with water or saline and protect the eye until sensation returns.

External Heat Sources

Placement of external heat sources, such as heating pads or electric blankets, over patches is not recommended as this has not been evaluated and may increase plasma Lidocaine levels.

Drug Interactions: Antiarrhythmic Drugs

Lidothol should be used with caution in patients receiving Class 1 antiarrhythmic drugs (such as tocainide and mexiletine) since the toxic effects are additive and potentially synergistic.

Local Anesthetics

When Lidothol is used concurrently with other products containing local anesthetic agents the amount absorbed from all formulations must be considered.

Carcinogenesis, Mutagenesis, Impairment of Fertility Carcinogenesis

A minor metabolite, 2,6-‐xylidine, has been found to be carcinogenic in rats. The blood concentration of this metabolite is negligible following application of Lidothol

Mutagenesis

Lidocaine is not mutagenic in Salmonella/mammalian microsome test nor clastogenic in chromosome aberration assay with human lymphocytes and mouse micronucleus test.

Impairment of Fertility

The effect of Lidothol on fertility has not been studied.

PREGNANCY:

The safety of Lidothol has not been established during pregnancy. There are no well-‐controlled studies in pregnant women. Lidothol should not be used during pregnancy unless absolutely needed. Discuss with physician prior to using Lidothol during pregnancy.

NURSING MOTHERS:

The effect of Lidothol on the nursing infant has not been evaluated. Lidothol has not been studied in nursing mothers. Caution should be exercised when Lidothol is administered to a nursing mother.

PEDIATRIC/GERIATRIC USE:

Safety and effectiveness in pediatric and geriatric patients have not been established.

ADVERSE REACTIONS:

The most common adverse reactions occur at the application site, including dermatitis, itching or scaling. These tend to be dose-‐limiting and diminish with time.

Serious adverse experiences following the administration of Lidothol are similar in nature to those observed in other amide anesthetic-‐containing agents. These adverse experiences are, in general, dose-‐related and may result from high plasma levels caused by excessive dosage, rapid absorption, or may result from hypersensitivity, idiosyncrasy, or a diminished tolerance on the part of the patient. Serious adverse experiences are generally systemic in nature. During or immediately after treatment with Lidothol, the skin at the site of application may develop redness, blisters, bruising, burning sensation, depigmentation, dermatitis, or mild irritation.

Allergic Reactions

Allergic and anaphylactoid reactions associated with Lidocaine, although rare, can occur. They are characterized by angioedema, bronchospasm, dermatitis, dyspnea, hypersensitivity, laryngospasm, pruritus, shock, and urticaria. If they occur, consult your doctor.

WARNINGS AND PRECAUTIONS

Methemoglobinemia

Cases of methemoglobinemia have been reported in association with local anesthetic use. Although all patients are at risk for methemoglobinemia, patients with glucose-6-phosphate dehydrogenase deficiency, congenital or idiopathic methemoglobinemia, cardiac or pulmonary compromise, infants under 6 months of age, and concurrent exposure to oxidizing agents or their metabolites are more susceptible to developing clinical manifestations of the condition. If local anesthetics must be used in these patients, close monitoring for symptoms and signs of methemoglobinemia is recommended.

Signs and symptoms of methemoglobinemia may occur immediately or may be delayed some hours after exposure and are characterized by a cyanotic skin discoloration and abnormal coloration of the blood. Methemoglobin levels may continue to rise; therefore, immediate treatment is required to avert more serious central nervous system and cardiovascular adverse effects, including seizures, coma, arrhythmias, and death. Discontinue Lidothol and any other oxidizing agents. Depending on the severity of the symptoms, patients may respond to supportive care, i.e., oxygen therapy, hydration. More severe symptoms may require treatment with methylene blue, exchange transfusion, or hyperbaric oxygen.

DRUG INTERACTIONS

Patients that are administered local anesthetics may be at increased risk of developing methemoglobinemia when concurrently exposed to the following oxidizing agents

Class

Nitrates/Nitrites

Local Anesthetics

Antineoplastic agents

Antibiotics

Antimalarials

Anticonvulsants

Other drugs

Examples

nitroglycerin, nitroprusside, nitric oxide, nitrous oxide

benzocaine, lidocaine, bupivacaine, mepivacaine, tetracaine, prilocaine, procaine, articaine, ropivacaine

cyclophosphamide, flutamide, rasburicase, ifosfamide, hydroxyurea

dapsone, sulfonamides, nitrofurantoin, para-aminosalicyclic acid

chloroquine, primaquine

phenytoin, sodium valproate, phenobarbital

acetaminophen, metoclopramide, sulfa drugs (i.e., sulfasalazine), quinine

DOSAGE AND ADMINISTRATION:

Apply Lidothol to intact skin to cover the most painful area. Apply no more than four patches per day. Each patch should not be applied for more than 12 hours in a given 24-‐ hour period. Patches may be cut into smaller sizes with scissors prior to removal of the protective film. Clothing may be worn over the area of application. Smaller areas of treatment are recommended in a debilitated patient, or a patient with impaired elimination.

If irritation or a burning sensation occurs during application, remove the patch and do not reapply until the irritation subsides.

When Lidothol is used concurrently with other products containing local anesthetic agents, the amount absorbed from all formulations must be considered.

Lidothol may not stick if it gets wet. Avoid contact with water, such as bathing, swimming or showering.

OVERDOSAGE:

There have been no reports of over-‐dosage with Lidothol. Signs of overdosage would include vomiting, drowsiness, coma, respiratory depression, and seizures. In the case of overdosage, discontinue the product immediately, treat the patient symptomatically, and institute supportive measures.

Lidothol is supplied in the following dosage form:

15 Patches: 5 per re-‐sealable pouch, 3 pouches

NDC 82881-441-15

Manufactured For:

Clinic Pharma
Las Vegas, NV 89121

HANDLING AND DISPOSAL:

Wash hands immediately after applying or removing Lidothol. Eye contact with Lidothol should be avoided. Do not store patch outside the sealed envelope. Apply immediately after removal from the protective envelope. Fold used patches so the adhesive side sticks to itself, then safely discard used patches or pieces of cut patches where children and pets cannot access them. Lidothol should be kept out of reach of children.

STORAGE:

Store at room temperature of 65˚F to 75˚F (18˚C to 24˚C). Keep away from heat or sunlight. Protect from excessive moisture. The product can be considered safe and effective to use when maintained under these recommended conditions within the posted expiration date.

PATIENT INFORMATION

Lidothol (Lidocaine 4% / Menthol 1% Patch)

For Topical Use Only

Do not use:

- On the face or rashes
- On wounds, damaged, or infected skin
- In the eyes, mouth or other mucous membranes
- On genitals
- With a heating pad

Ask a doctor before use if:

- You are allergic to topical products or any ingredients in this product
- You are pregnant or breast feeding
- You are under age 18

When using this product:

- Wash hands after applying or removing patch
- Avoid contact with eyes
- If eye contact occurs, rinse thoroughly with water

Stop use and consult your physician if:

- Rash, irritation, or itching develops
- Condition worsens

Keep out of reach of children

Lidothol Patient Information.

Before you begin using this medication: read this entire patient information sheet. If you have any questions, please consult your physician or pharmacist. Inform your physician if your condition does not improve or if it worsens.

This information may not include all of the details needed to use Lidothol safely and effectively. Discuss use with your doctor or pharmacist.

What is Lidothol?

A topical pain relief patch consisting of the local anesthetic Lidocaine (4%) and the topical analgesic Menthol (1%).

What is Lidothol used for?

The patch assists patients in the management of mild to moderate acute pain or mild to moderate aches. Lidothol is applied to the skin at the specific region experiencing these pain symptoms. The synthesis of Lidocaine and Menthol is a highly effective combination of pain relievers working to alleviate discomfort while the root cause is being managed and treated by your healthcare providers.

DO NOT USE:

- If you are allergic to any of the ingredients in this product
- On wounds or damaged skin
- With a heating pad
- If you are pregnant, planning to become pregnant, or breastfeeding

What are the possible side effects with Lidothol?

- Common: itching or redness of the skin following application
- NOTE: The majority of patients experience no significant adverse events following patch application. Serious side effects, are, in general, related to accidental toxicity of medication by applying considerably more than directed by your doctor or pharmacist or by ingesting the contents of the patch.
- Tell your healthcare provider about all the medicines you take. This includes prescription and nonprescription medicines, vitamins, and herbal supplements.
- Avoid excessive alcohol usage, since it may increase the potential for Central Nervous System (CNS) effects such as dizziness, confusion, lightheadedness and orthostatic hypotension.

This is not a complete list of the possible side effects. For more information, talk with your doctor or pharmacist. You may report side effects to FDA at 1-‐800-FDA-1088 or www.fda.gov/medwatch

KEEP OUT OF REACH OF CHILDREN Rx ONLY

DIRECTIONS FOR USE

Adults and children 12 years and over:

Apply 1 to 2 patches to the affected area of intact skin. Lidothol should be removed after 12 hours of continuous use and remain off for at least 12 hours.

1. Determine area of patch application. If the pain area is smaller than the patch, patches may be cut into smaller sizes with scissors. Safely discard the remaining unused pieces of cut patches where children and pets cannot reach.
2. Remove the transparent protective film (clear plastic barrier) before application of patches to the skin. Apply immediately after removing the protective film.
3. Apply 1 patch to the affected area so that the patch covers all or most of the painful area.
4. Remove patch if irritation occurs.

Children under 12 years of age: Consult a doctor

WARNINGS

1. Do not use:

- On wounds, cuts, damaged or infected skin
- On eyes, mouth, genitals, or other mucous membranes

2. Consult physician for children under 12 years of age

3. Stop and consult your prescriber if pain worsens

Call your healthcare provider right away if you experience any of the following warning signs or any other unusual symptoms of concern:

- Shortness of breath
- Swelling or numbness of the tongue or throat
- Severe headache or vomiting
- Dizziness or faintness
- Changes in vision or speech

General information for safe and effective use of Lidothol

Do not use this product for another indication. Do not give this drug to anyone else, even if they have the same condition. This product is intended for use as prescribed by a physician.

How should I store Lidothol?

Store product at room temperature at 65˚F to 75˚F (18˚C to 24˚C). Keep away from heat or sunlight. Protect from excessive moisture. Safely discard product after expiration date posted on the product label. Discard patches away from small children or animals.

DO NOT use the product after the expiration date printed on the box.

This insert provides the most important information about Lidothol. If you would like more information, talk with your healthcare provider or pharmacist. There is additional information in the following sections intended for healthcare professionals.

What are the active ingredients in Lidothol?

The patch consists of 4% Lidocaine and 1% Menthol.

What are the inactive Ingredients in Lidothol?

dihydroxyaluminum aminoacetate, glycerol, methylparaben, polysorbate 80, propylene glycol, sodium polyacrylate, tartaric acid, water